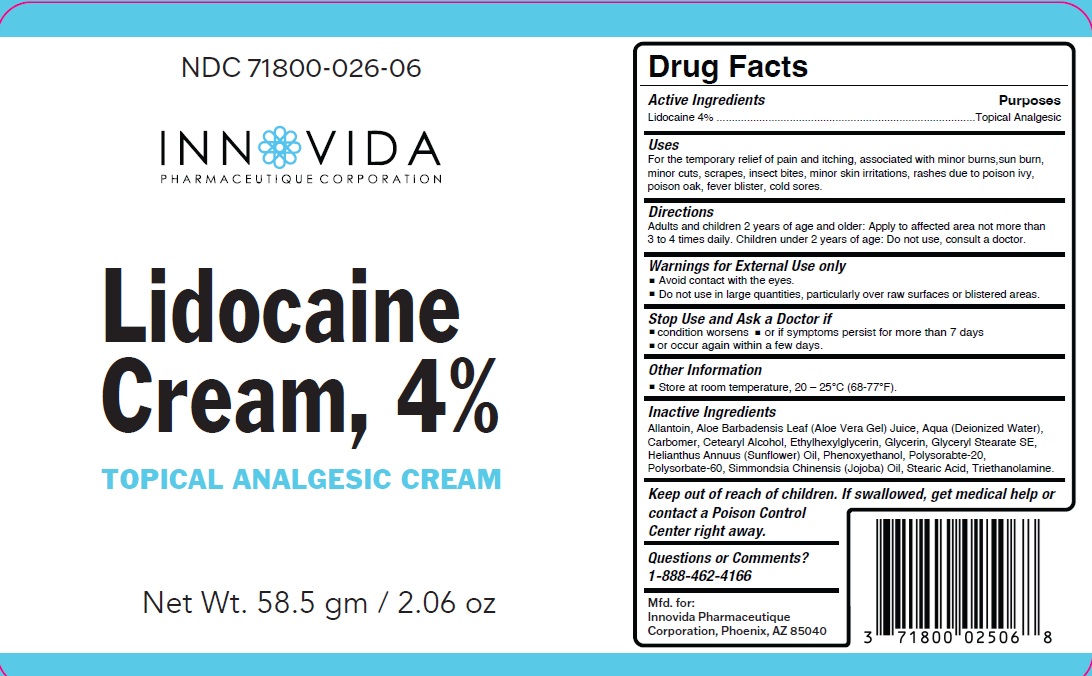 DRUG LABEL: Lidocaine 4%
NDC: 71800-026 | Form: CREAM
Manufacturer: Innovida Pharmaeutique Corporation
Category: otc | Type: HUMAN OTC DRUG LABEL
Date: 20250319

ACTIVE INGREDIENTS: LIDOCAINE 4 g/100 g
INACTIVE INGREDIENTS: ALLANTOIN; ALOE VERA LEAF; WATER; CARBOMER; CETOSTEARYL ALCOHOL; ETHYLHEXYLGLYCERIN; GLYCERIN; GLYCERYL STEARATE SE; HELIANTHUS ANNUUS FLOWERING TOP; PHENOXYETHANOL; POLYSORBATE 20; POLYSORBATE 60; SIMMONDSIA CHINENSIS LEAF; STEARIC ACID; TROLAMINE

Active Ingredient

Lidocaine 4%

Purpose

Topical Analgesic

Uses

For the temporary relief of pain and itching, associated with minor burns,sun burn, minor cuts, scrapes, insect bites, minor skin irritations, rashes due to poison ivy, poison oak, fever blister, cold sores.

Warnings

For external Use only

- Avoid contact with the eyes.
- Do not use in large quantities, particularly over raw surfaces or blistered areas.

Stop Use and Ask a Doctor if

- condition worsens or if symptoms persist for more than 7 days
- or occur again within a few days.

Keep out of reach of children. If swallowed, get medical help or contact a Poison Control Center right away.

Directions

Adults and children 2 years of age and older: Apply to affected area not more than 3 to 4 times daily. Children under 2 years of age: Do not use, consult a doctor.

Other information

Store at room temperature, 20 – 25°C (68-77°F).

Inactive Ingredients

Allantoin, Aloe Barbadensis Leaf (Aloe Vera Gel) Juice, Aqua (Deionized Water),Carbomer, Cetearyl Alcohol, Ethylhexylglycerin, Glycerin, Glyceryl Stearate SE,Helianthus Annuus (Sunflower) Oil, Phenoxyethanol, Polysorabte-20, Polysorbate-60, Simmondsia Chinensis (Jojoba) Oil, Stearic Acid, Triethanolamine.